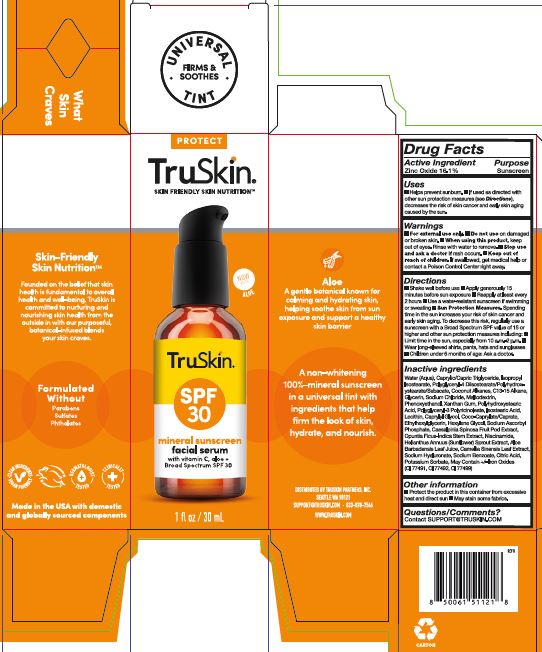 DRUG LABEL: Truskin Broad Spectrum Mineral Sunscreen Facial Serum with Vitamin C and Aloe
NDC: 62742-4275 | Form: CREAM
Manufacturer: Allure Labs
Category: otc | Type: HUMAN OTC DRUG LABEL
Date: 20251106

ACTIVE INGREDIENTS: ZINC OXIDE 16.1 g/100 g
INACTIVE INGREDIENTS: XANTHAN GUM; LECITHIN, SUNFLOWER; SODIUM HYALURONATE; NIACINAMIDE; WATER; MALTODEXTRIN; CAMELLIA SINENSIS LEAF; CI 77492; C13-15 ALKANE; COCO-CAPRYLATE/CAPRATE; HEXYLENE GLYCOL; CAESALPINIA SPINOSA FRUIT POD; POLYHYDROXYSTEARIC ACID (2300 MW); POLYGLYCERYL-3 PENTARICINOLEATE; HELIANTHUS ANNUUS SPROUT; CI 77491; PHENOXYETHANOL; CAPRYLYL GLYCOL; SODIUM CHLORIDE; ISOSTEARIC ACID; CITRIC ACID; ALOE BARBADENSIS LEAF JUICE; CAPRYLIC/CAPRIC TRIGLYCERIDE; POTASSIUM SORBATE; ISOPROPYL ISOSTEARATE; SODIUM BENZOATE; GLYCERIN; CI 77499; ETHYLHEXYLGLYCERIN; SODIUM ASCORBYL PHOSPHATE; POLYGLYCERYL-4 DIISOSTEARATE/POLYHYDROXYSTEARATE/SEBACATE; COCONUT ALKANES; OPUNTIA FICUS-INDICA STEM

Drug Facts

Active ingredients: Zinc Oxide 16.1%

Purpose: Sunscreen

INDICATIONS AND USAGE

Uses ■ Helps prevent sunburn. ■ If used as directed with other sun protection measures (see Directions), decreases the risk of skin cancer and early skin aging caused by the sun.

WARNINGS

For external use only.

Do not use on damaged or broken skin.

when using this product, keep out of eyes. Rinse with water to remove.

Stop use and ask a doctor if rash occurs.

keep out of reach of children. If swallowed, get medical help or contact a Poison Control Center right away.

DOSAGE AND ADMINISTRATION

Directions ■ Shake well before use ■ Apply generously 15 minutes before sun exposure ■ Reapply at least every 2 hours ■ Use a water-resistant sunscreen if swimming or sweating ■ Sun Protection Measures Spending time in the sun increases your risk of skin cancer and early skin aging. To decrease this risk, regularly use sunscreen with a Broad Spectrum SPF value of 15 or higher and other sun protection measures including ■ Limit time in the sun, especially from 10 a.m.-2 p.m. ■ Wear long-sleeved shirts, pants hats and sunglasses ■ Children under 6 months of age: Ask a doctor.

OTHER SAFETY INFORMATION

Protect the product in this container from excessive heat and direct sun. May stain some fabrics.

Inactive Ingredients:
Water(Aqua),Caprylic/capric Triglyceride, Isopropyl Isostearate, Polyglyceryl -4 Diisostearate/Polyhydroxy stearate/sebacate, Coconut Alkanes, C13-15 Alkane, Glycerin, Sodium Chloride, Maltodextrin, Phenoxyethanol, Xanthan Gum, Polyhydroxystearic acid, Polyglyceryl – 3 Polyricinoleate, Isosteric acid, Lecithin, Caprylyl Glycol, Coco-Caprylate/-Caprate, Ethylhexylglycerin, Hexylene Glycol, Sodium Ascorbyl Phosphate, Caesalpinia Spinosa Fruit Pod Extract, Opuntia Ficus-Indica Stem Extract, Niacinamide, Helianthus Annuus (Sunflower) Sprout Extract,Aloe Barbadensis Leaf Juice, Camellia Sinensis Leaf Extract, Sodium Hyaluronate, Sodium Benzoate, Citric Acid, Potassium Sorbate, May Contain +/_ Iron oxides (CI77491, CI77492, CI 77499)